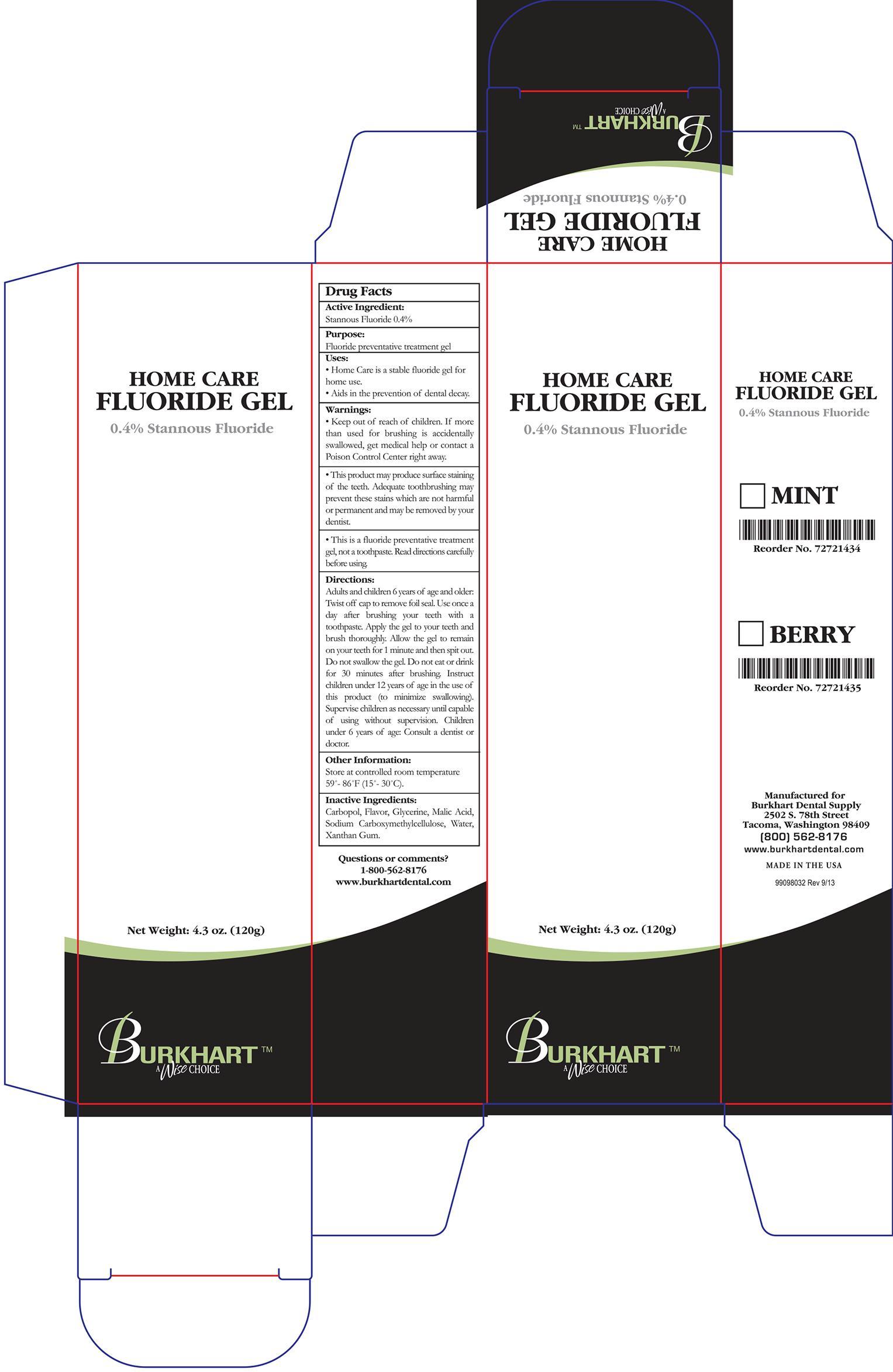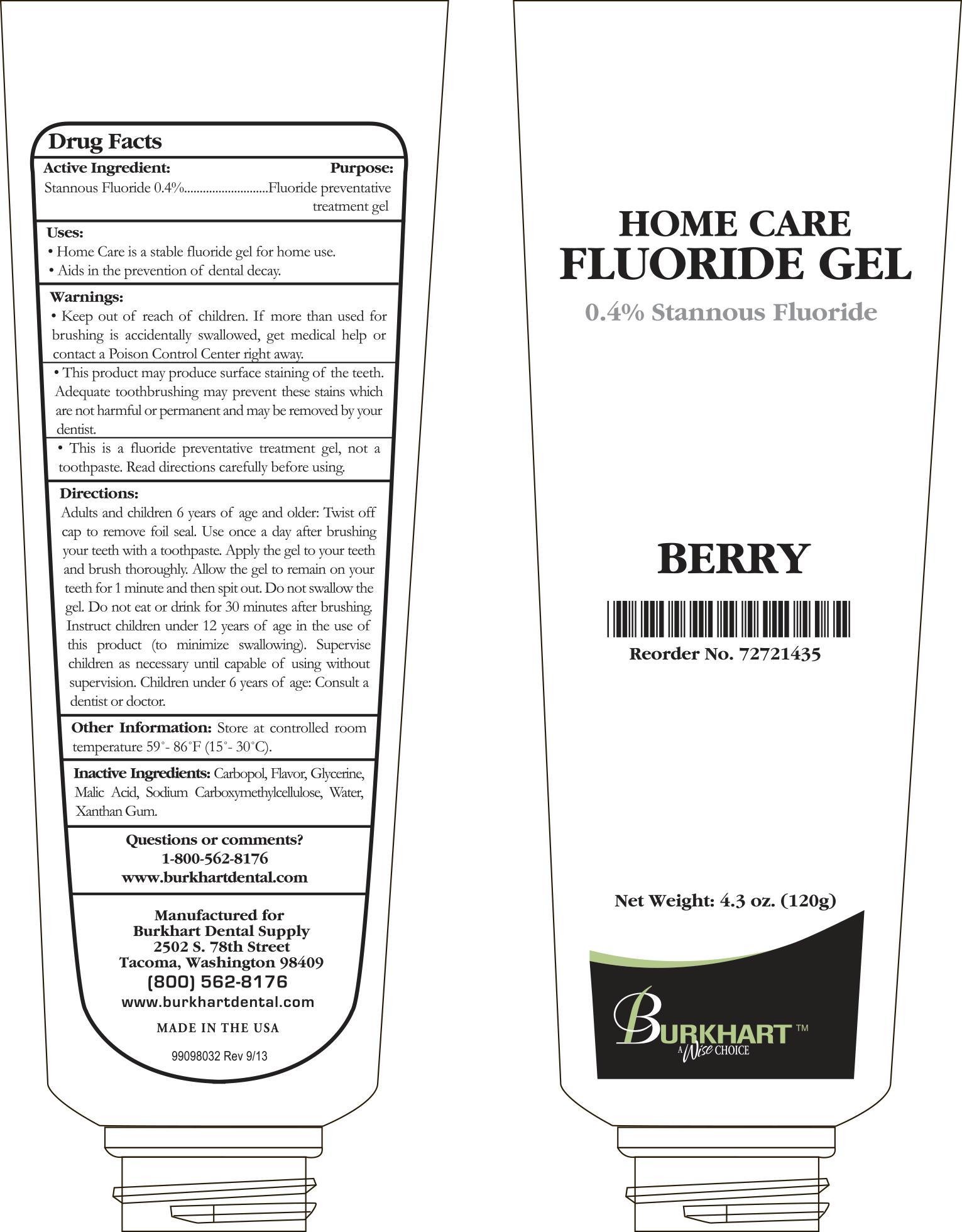 DRUG LABEL: Burkhart
NDC: 43498-251 | Form: GEL
Manufacturer: Burkhart Dental Supply Inc
Category: otc | Type: HUMAN OTC DRUG LABEL
Date: 20250109

ACTIVE INGREDIENTS: STANNOUS FLUORIDE 0.116 g/120 g
INACTIVE INGREDIENTS: GLYCERIN; WATER; CARBOMER HOMOPOLYMER TYPE C (ALLYL PENTAERYTHRITOL CROSSLINKED); CARBOXYMETHYLCELLULOSE SODIUM; MALIC ACID; XANTHAN GUM

Active Ingredient:

Stannous Fluoride 0.4%

Purpose:

Fluoride preventive treatment gel.

Uses:

- Home Care is a stable, water-free fluoride gel for home use.
- Aids in the prevention of dental decay.

Keep out of reach of children.

Warnings:

- If more than used for brushing is accidentally swallowed, get medical help or contact a Poison Control Center right away.
- This product may produce surface staining of the teeth. Adequate toothbrushing may prevent these stains which are not harmful or permanent and may be removed by your dentist.
- This is a fluoride preventive treatment gel, not a toothpaste. Read directions carefully before using.

Directions:

Adults and children 6 years of age and older: Twist off cap and remove foil seal. Use once a day after brushing your teeth with a toothpaste. Apply the gel to your teeth and brush thoroughly. Allow the gel to remain on your teeth for 1 minute and then spit out. Do not swallow the gel. Do not eat or drink for 30 minutes after brushing. Instruct children under 12 years of age in the use of this product (to minimize swallowing). Supervise children as necessary until capable of using without supervision. Children under 6 years of age: consult a dentist or doctor.

Other Information:

Store at controlled room temperature 59° - 86°F (15° - 30°C)

Inactive Ingredients:

Carbopol, Flavor, Glycerine, Malic Acid, Sodium Carboxymethylcellulose, Water, Xanthan Gum.